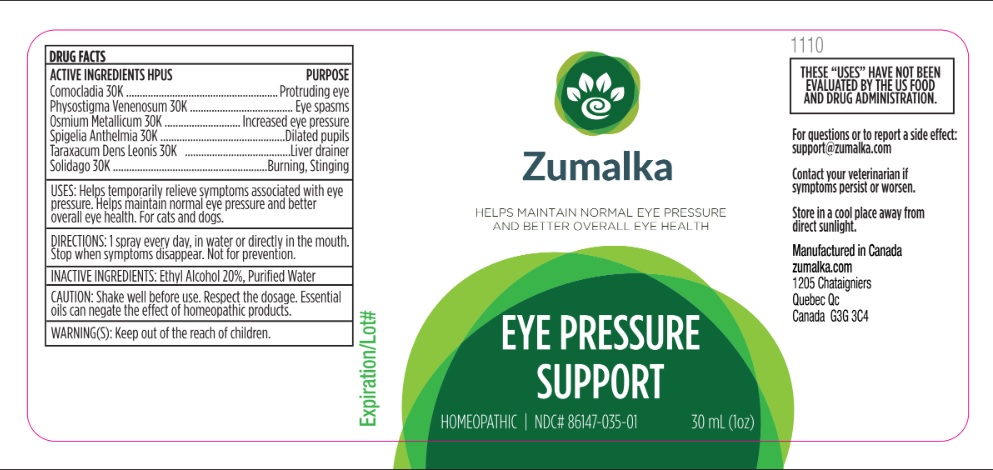 DRUG LABEL: EYE PRESSURE SUPPORT
NDC: 86147-035 | Form: LIQUID
Manufacturer: Groupe Cyrenne Inc.
Category: homeopathic | Type: OTC ANIMAL DRUG LABEL
Date: 20251120

ACTIVE INGREDIENTS: COMOCLADIA DENTATA BARK/LEAF 30 [kp_C]/30 mL; PHYSOSTIGMA VENENOSUM SEED 30 [kp_C]/30 mL; OSMIUM 30 [kp_C]/30 mL; SPIGELIA ANTHELMIA WHOLE 30 [kp_C]/30 mL; TARAXACUM PALUSTRE ROOT 30 [kp_C]/30 mL; SOLIDAGO VIRGAUREA FLOWERING TOP 30 [kp_C]/30 mL
INACTIVE INGREDIENTS: ALCOHOL; WATER

Active ingredients Purpose

Comocladia 30k Protruding eye

Physostigma Venenosum 30k Eye spasms

Osmium Metallicum 30k Increased eye pressure

Spigelia Anthelmia 30k Dilated pupils

Taraxacum Dens Leonis 30k Liver drainer

Solidago 30k Burning, Stinging

Uses

Helps temporarily relieve symptoms associated with eye pressure. Helps maintain normal eye pressure and better overall eye health. For cats and dogs.

Warnings

Keep out of reach of children.

Direction

1 spray every day, in water or directly in the mouth. Stop when symptoms disappear. Not for prevention.

Inactive ingredients

Ethyl alcohol 20%, purified water

Cautions

Shake well before use. Respect the dosage. Essential oils can negate the effects of homeopathic products. Store in a cool place away from direct sunlight.